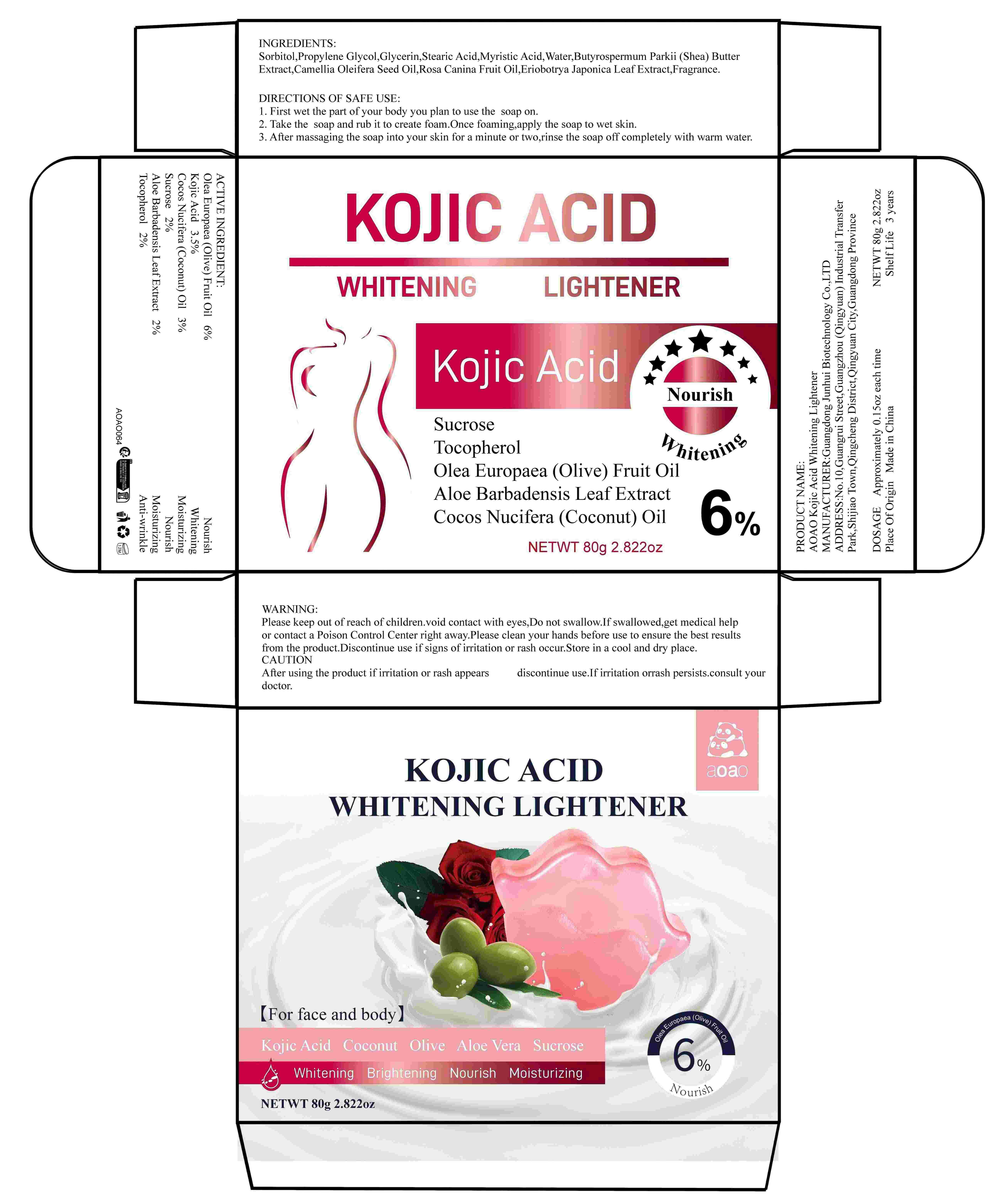 DRUG LABEL: AOAO Kojic Acid Whitening Lightener
NDC: 84509-049 | Form: SOAP
Manufacturer: Guangdong Junhui Biotechnology Co., LTD
Category: otc | Type: HUMAN OTC DRUG LABEL
Date: 20241112

ACTIVE INGREDIENTS: OLEA EUROPAEA (OLIVE) FRUIT OIL 4800 mg/80 g; SUCROSE 1600 mg/80 g; COCOS NUCIFERA (COCONUT) OIL 2400 mg/80 g; KOJIC ACID 2800 mg/80 g; ALOE BARBADENSIS LEAF EXTRACT 1600 mg/80 g; TOCOPHEROL 1600 mg/80 g
INACTIVE INGREDIENTS: MYRISTIC ACID; CAMELLIA OLEIFERA SEED OIL; GLYCERIN; WATER; ROSA CANINA FRUIT OIL; FRAGRANCE 13576; ERIOBOTRYA JAPONICA LEAF EXTRACT; PROPYLENE GLYCOL; STEARIC ACID; SORBITOL; BUTYROSPERMUM PARKII (SHEA) BUTTER EXTRACT

Active Ingredients

Olea Europaea (Olive) Fruit Oil 6%
Kojic Acid 3.5%
Cocos Nucifera (Coconut) Oil 3%
Sucrose 2%
Aloe Barbadensis Leaf Extract 2%
Tocopherol 2%

Purpose

nourish
Whitening
Moisturizing
Exfoliating
Moisturizing
Anti-wrinkle

Uses

DIRECTIONS OF SAFE USE：
1. First wet the part of your body you plan to use the exfoliating soap on.
2. Take the exfoliating soap and rub it to create foam. Once foaming, apply the soap to wet skin.
3. After massaging the soap into your skin for a minute or two, rinse the soap off completely with warm water.

Warnings

For external use only. Keep out ofreach of children.Avoid contact with eyes

Keep out of reach of children

If swallowed, get medical help or contact a Poison Control Center right away

CAUTION

After using the product if irritation or rash appears,discontinue use.If irritation or
rash persists.consult your doctor.

Inactive Ingredients

Sorbitol,Propylene Glycol,Glycerin,Stearic Acid,Myristic Acid, Water,Butyrospermum Parkii (Shea) Butter Extract,Camellia Oleifera Seed Oil,Rosa Canina Fruit Oil,Eriobotrya Japonica Leaf Extract,Fragrance

Product Name

AOAO Kojic Acid Whitening Lightener

DOSAGE

Approximately 0.15oz each time

Manufacturer

Guangdong Junhui Biotechnology Co., LTD

ADDRESS

No. 10, Guangrui Street, Guangzhou (Qingyuan) Industrial Transfer Park, Shijiao Town, Qingcheng District, Qingyuan City, Guangdong Province

Capacity

NETWT 80g 2.822oz

Shelf Life

3 Years

Place of Origin

Made in China